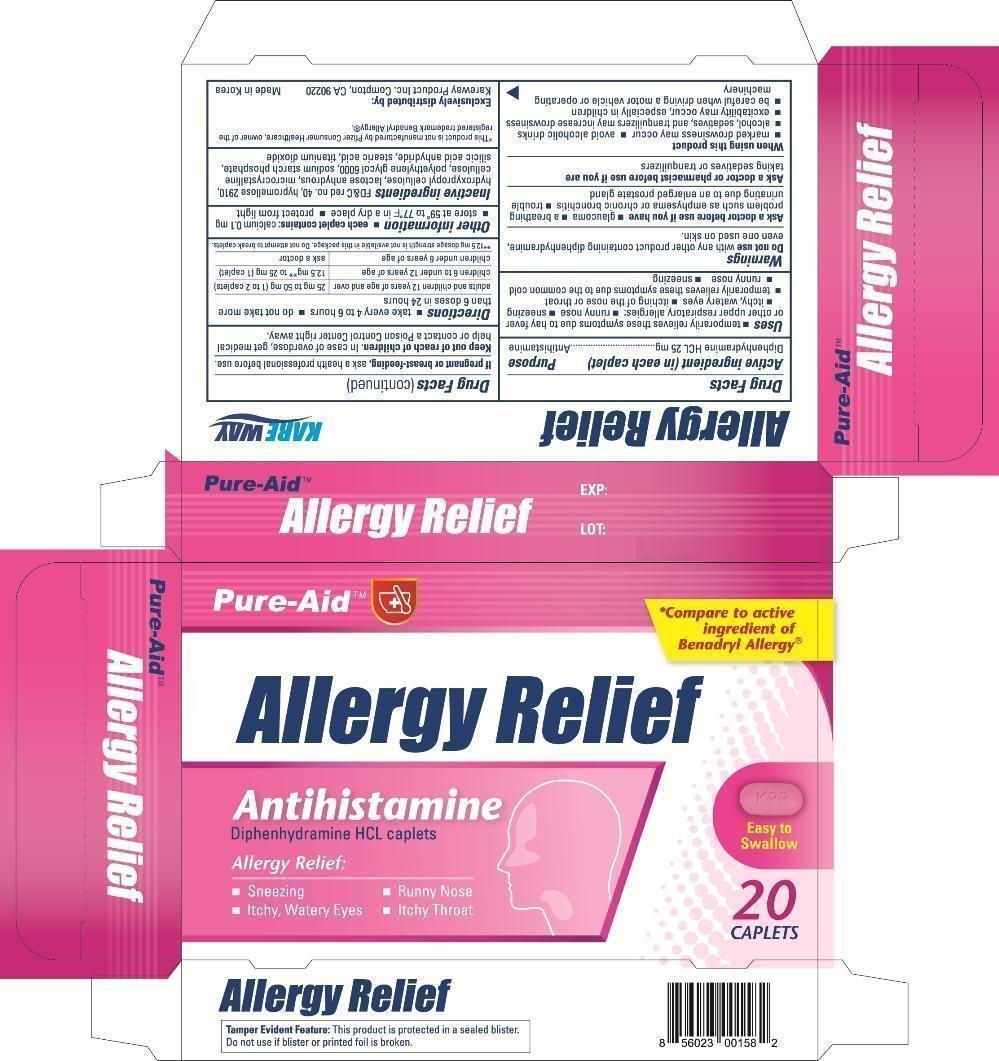 DRUG LABEL: Allergy Relief
NDC: 67510-0158 | Form: TABLET
Manufacturer: Kareway Product, Inc.
Category: otc | Type: HUMAN OTC DRUG LABEL
Date: 20130215

ACTIVE INGREDIENTS: DIPHENHYDRAMINE HYDROCHLORIDE 25 mg/1 1
INACTIVE INGREDIENTS: MICROCRYSTALLINE WAX; ANHYDROUS LACTOSE; SODIUM STARCH GLYCOLATE TYPE A POTATO; STARCH, CORN; DIBASIC CALCIUM PHOSPHATE DIHYDRATE; CROSPOVIDONE; STEARIC ACID; MAGNESIUM STEARATE; HYPROMELLOSES; FD&C RED NO. 3; POLYETHYLENE GLYCOLS; TITANIUM DIOXIDE; ETHANETHIOL

Drug Facts

Active ingredient (in each tablet)

Diphenhydramine HCL 25mg

Purpose

Antihistamine

Uses

- temporarily relieves these symptoms due to hay fever or other upper respiratory allergies:
-
  - runny nose
-
  - sneezing
  - itchy, watery eyes
  - itching of the nose or throat
- temporarily relieves these symptoms due to the common cold
-
  - runny nose
-
  - sneezing

Warnings

Do not use with any other product containing diphenhydramine, even one used on skin

Ask a doctor before use if you have

- glaucoma
- a breathing problem such as emphysema or chronic bronchitis
- trouble urinating due to an enlarged prostate gland

Ask a doctor or pharmacist before use if you are

taking sedatives or tranquilizers

When using this product

- marked drowsiness may occur
- avoid alcoholic drinks
- alcohol, sedatives, and tranquilizers may increase drowsiness
- excitability may occur, especially in children
- be careful when driving a motor vehicle or operating machinery

If pregnant or breast-feeding,

ask a health professional before use.

Keep out of reach of children.

In case of accidental overdose get medical help or contact a Poison Control Center right away.

Directions

- take every 4 to 6 hours
- do not take more than 6 doses in 24 hours

adults and children 12 years of age and over | 25 mg to 50 mg (1 to 2 tablets)
children 6 to under 12 years of age | 12.5** to 25 mg (1 tablet)
children under 6 years of age | ask a doctor

**12.5 mg dosage strength is not available in this package. Do not attempt to break tablets.

Other information

- each tablet contains:calcium 0.1mg
- store at 59° to 77°F in a dry place
- protect from light

Inactive ingredients

microcrystalline cellulose, lactose anhydrous, sodium starch glycolate, pregelatinized starch, dibasic calcium phosphate dihydrate, crospovidone, stearic acid, magnesium stearate, hypromellose, polyethyleneglycol, titanium dioxide, ethanol

Package label

Allergy Relief